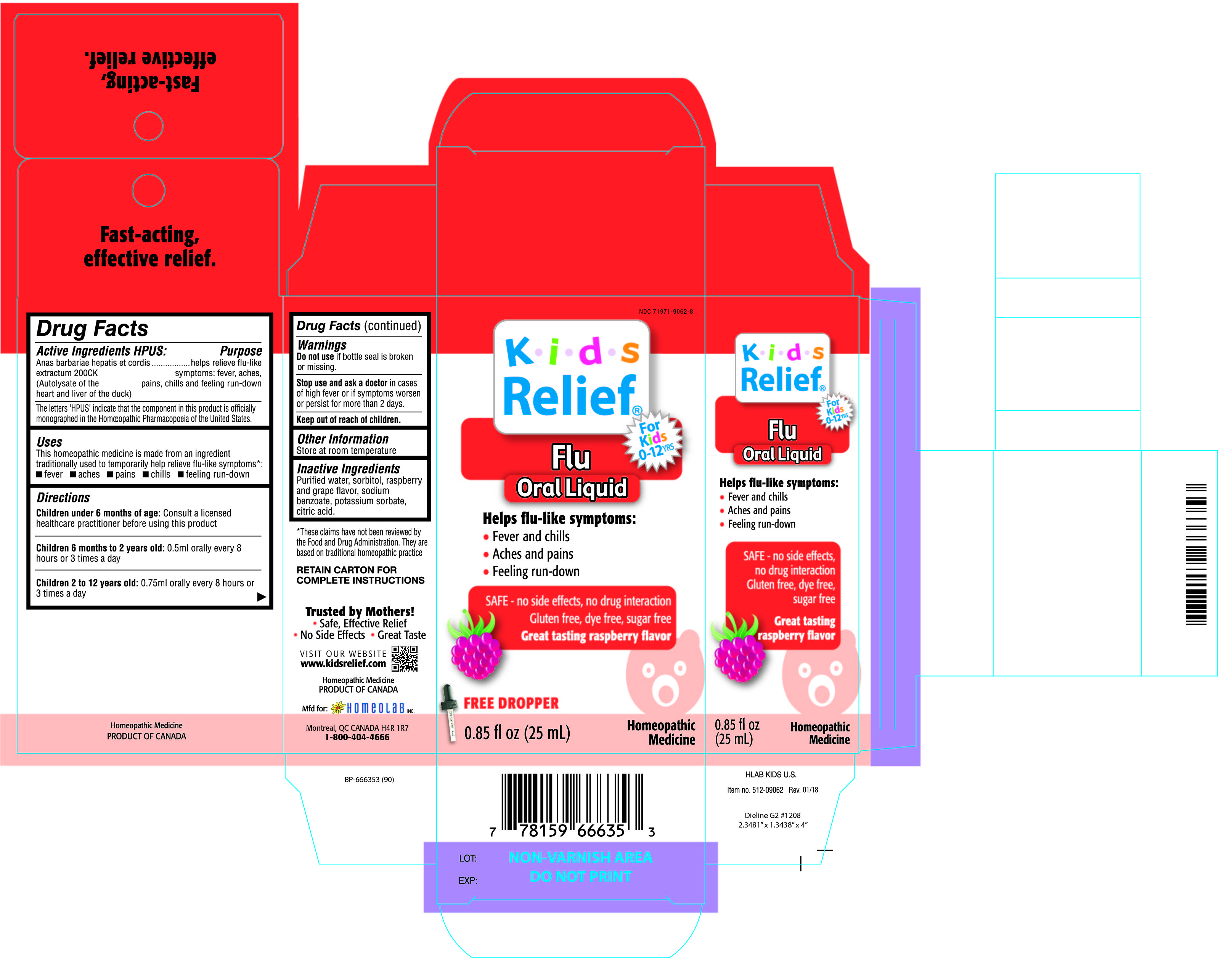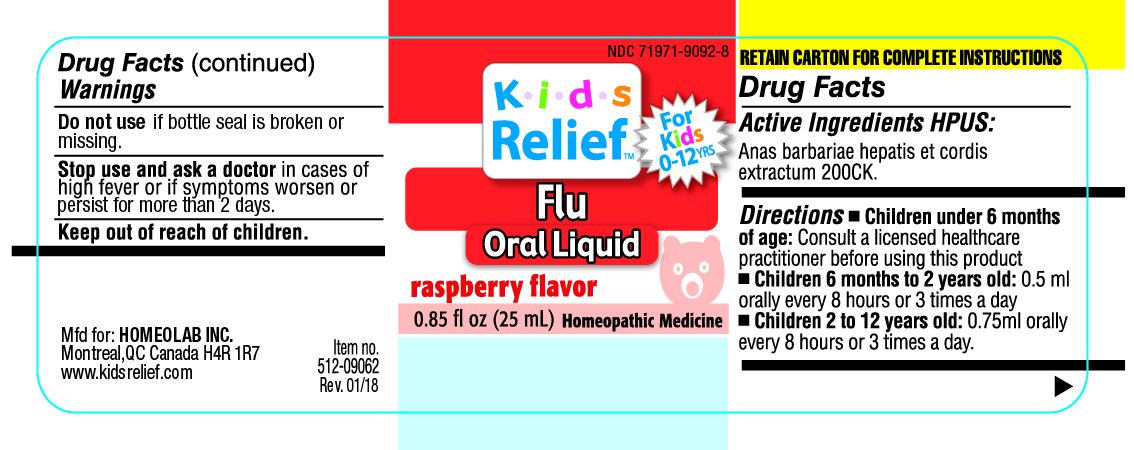 DRUG LABEL: Kids Relief
NDC: 71971-9062 | Form: LIQUID
Manufacturer: Homeolab International (Canada) inc
Category: homeopathic | Type: HUMAN OTC DRUG LABEL
Date: 20190716

ACTIVE INGREDIENTS: CAIRINA MOSCHATA HEART/LIVER AUTOLYSATE 200 [hp_C]/25 mL
INACTIVE INGREDIENTS: WATER; SORBITOL; SODIUM BENZOATE; POTASSIUM SORBATE; CITRIC ACID ACETATE

Active ingredients HPUS:

Anas barbariae hepatis et cordis

extractum 200 CK

(Autolysate of the

heart and liver of the duck)

The letters 'HPUS' indicate that the component in this product is officially

monographed in the Homeopathic Pharmacopoeia of the United States)

Purpose

helps relieve flu-like

symptoms; fever, aches.

pains. chillsand feeling run-down

Uses

This homeopathic medicine is made form an ingredient

traditionally used to temporarily help relieve flu-like symptoms*:

•fever •aches •pains •chills •feeling run-down

Directions

Children under 6 months of age: Consult a licensed

healthcare practitioner before using this product

Children 6 months to 2 years old: 0.5 ml orally every 8

hours or 3 times a day

Children 2 to 12 years old: 0.75 ml orally every 8 hours or

3 times a day

Warnings

Do not use if bottle seal is broken

or missing.

Stop use and ask a doctor in cases

of high fever or if symptoms worsen

or persist for more than 2 days.

Keep out of reach of children.

Other Information

Store at room temperature

Inactive Ingredients

Purified water, sorbitol, raspberry

and grape flavor, sodium

benzoate, potassium sorbate,

citric acid.